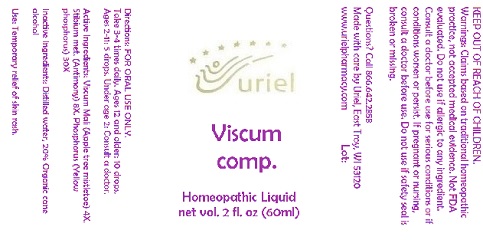 DRUG LABEL: Viscum comp.
NDC: 48951-9122 | Form: LIQUID
Manufacturer: Uriel Pharmacy Inc.
Category: homeopathic | Type: HUMAN OTC DRUG LABEL
Date: 20180510

ACTIVE INGREDIENTS: VISCUM ALBUM FRUITING TOP 4 [hp_X]/1 mL; ANTIMONY 8 [hp_X]/1 mL; PHOSPHORUS 30 [hp_X]/1 mL
INACTIVE INGREDIENTS: WATER; ALCOHOL

Viscum comp.

INDICATIONS AND USAGE

Directions: FOR ORAL USE ONLY.

DOSAGE AND ADMINISTRATION

Take 3-4 times daily. Ages 12 and older: 10 drops. Ages 2-11: 5 drops. Under age 2: Consult a doctor.

ACTIVE INGREDIENT

Active Ingredients: Viscum Mali (Apple tree mistletoe) 4X, Stibium met. (Antimony) 8X, Phosphorus (Yellow phosphorus) 30X

Inactive Ingredients: Distilled water, 20% Organic cane alcohol

PURPOSE

Use: Temporary relief of skin rash.

KEEP OUT OF REACH OF CHILDREN.

WARNINGS

Warnings: Claims based on traditional homeopathic practice, not accepted medical evidence. Not FDA evaluated. Do not use if allergic to any ingredient. Consult a doctor before use for serious conditions or if conditions worsen or persist. If pregnant or nursing, consult a doctor before use. Do not use if safety seal is broken or missing.

QUESTIONS

Questions? Call 866.642.2858 Made with care by Uriel, East Troy, WI 53120 www.urielpharmacy.com